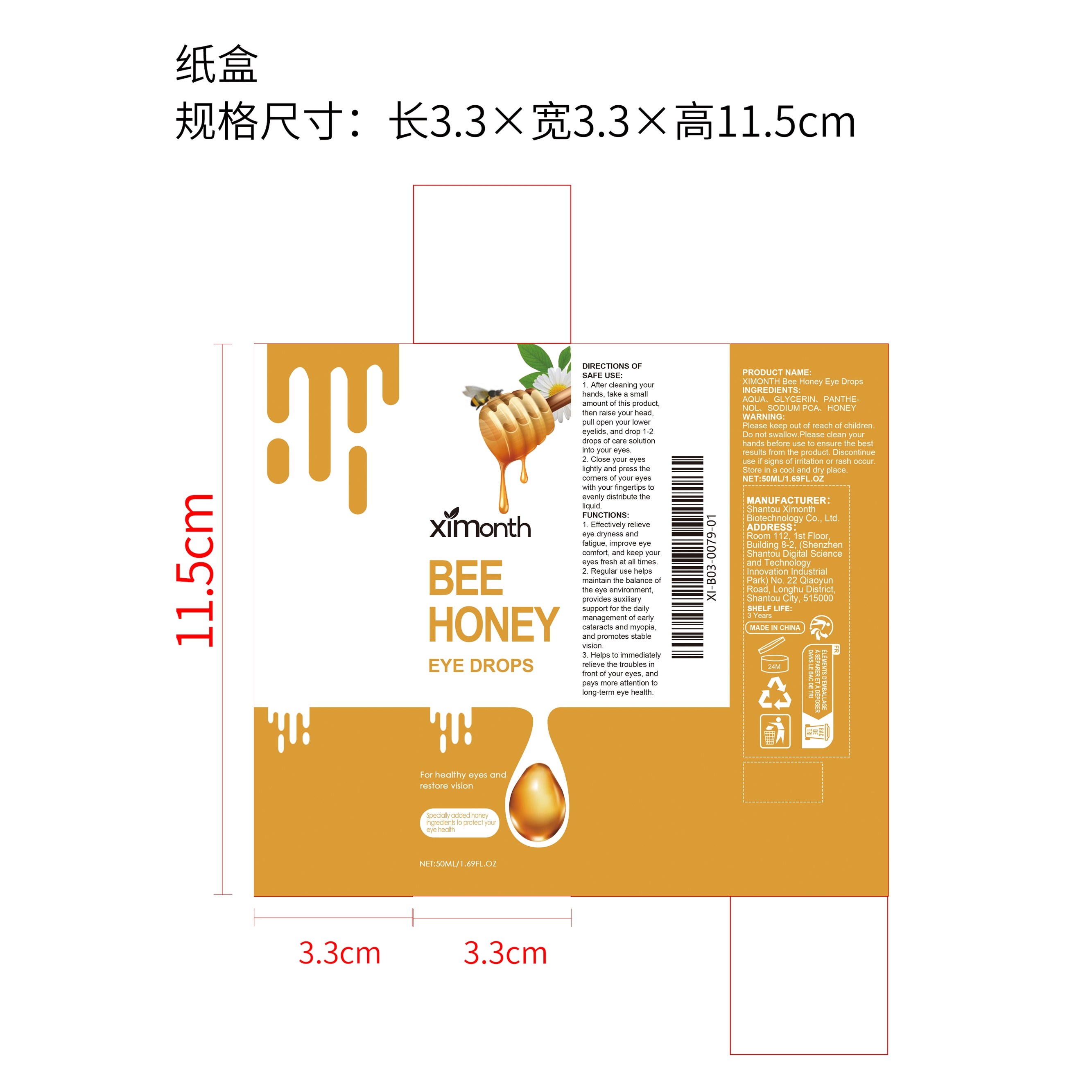 DRUG LABEL: XIMONTH Bee Honey Eye Drops
NDC: 84989-011 | Form: LIQUID
Manufacturer: Shantou Ximonth Biotechnology Co., Ltd.
Category: otc | Type: HUMAN OTC DRUG LABEL
Date: 20251126

ACTIVE INGREDIENTS: HONEY 0.01 mg/50 mg
INACTIVE INGREDIENTS: GLYCERIN 2 mg/50 mg; AQUA 46.74 mg/50 mg; PANTHENOL 0.75 mg/50 mg; SODIUM PCA 0.5 mg/50 mg

ACTIVE INGREDIENT

HONEY

PURPOSE

1. Effectively relieve eye dryness and fatigue, improve eye comfort, and keep your eyes fresh at all times.

2. Regular use helps maintain the balance of the eye environment, provides auxiliary support for the daily management of early cataracts and myopia, and promotes stable vision.

3. Helps to immediately relieve the troubles in front of your eyes, and pays more attention to long-term eye health.

WHEN USING

1. After cleaning your hands, take a small amount of this product, then raise your head, pull open your lower eyelids, and drop 1-2 drops of care solution into your eyes.

2. Close your eyes lightly and press the corners of your eyes with your fingertips to evenly distribute the liquid.

WARNINGS

Please keep out of reach of children. Do not swallow.Please clean your hands before use to ensure the best results from the product. Discontinue use if signs of irritation or rash occur. Store in a cool and dry place.

DO NOT USE

Discontinue use if signs of irritation or rash occur.

STOP USE

Discontinue use if signs of irritation or rash occur.

KEEP OUT OF REACH OF CHILDREN

Please keep out of reach of children. Do not swallow.

STORAGE AND HANDLING

Store in a cool and dry place.

INACTIVE INGREDIENT

AQUA、GLYCERIN、PANTHENOL、SODIUM PCA

DOSAGE AND ADMINISTRATION

1. After cleaning your hands, take a small amount of this product, then raise your head, pull open your lower eyelids, and drop 1-2 drops of care solution into your eyes.

2. Close your eyes lightly and press the corners of your eyes with your fingertips to evenly distribute the liquid.

INDICATIONS AND USAGE

1. Effectively relieve eye dryness and fatigue, improve eye comfort, and keep your eyes fresh at all times.

2. Regular use helps maintain the balance of the eye environment, provides auxiliary support for the daily management of early cataracts and myopia, and promotes stable vision.

3. Helps to immediately relieve the troubles in front of your eyes, and pays more attention to